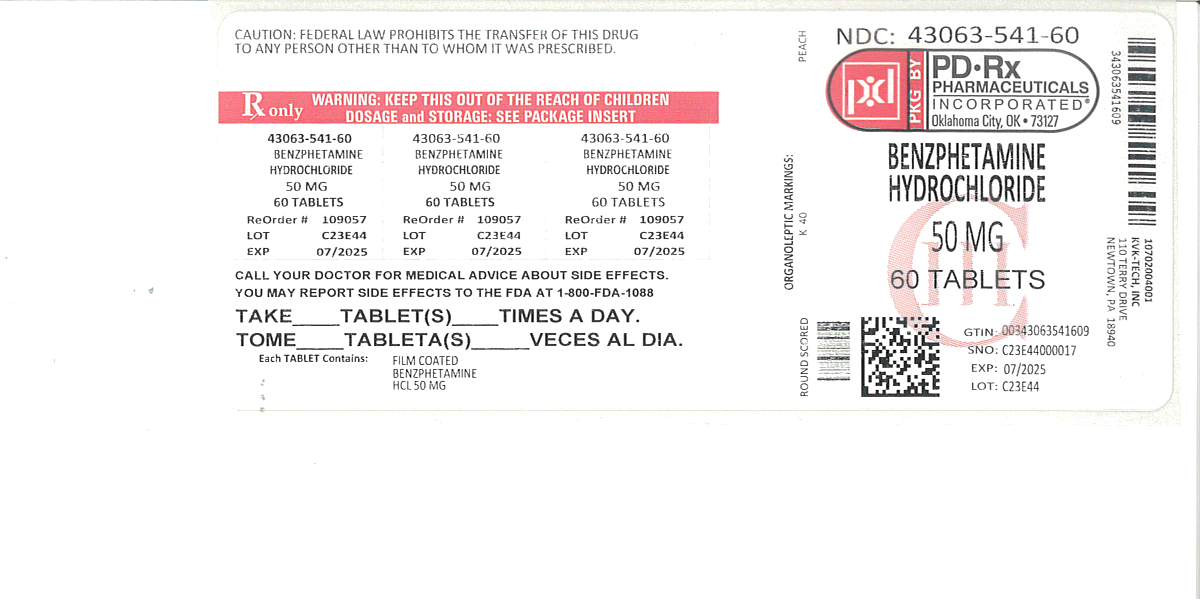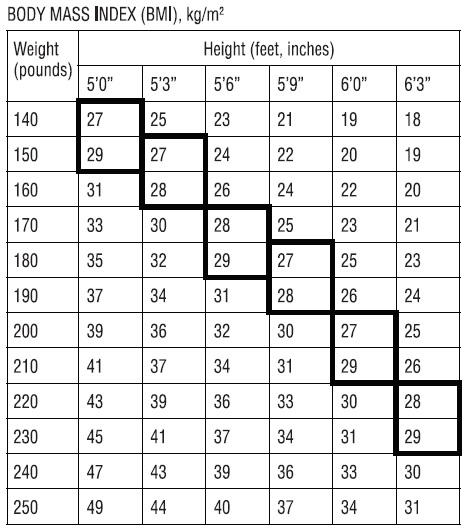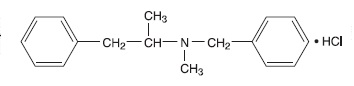 DRUG LABEL: BENZPHETAMINE HYDROCHLORIDE
NDC: 43063-541 | Form: TABLET
Manufacturer: PD-Rx Pharmaceuticals, Inc.
Category: prescription | Type: HUMAN PRESCRIPTION DRUG LABEL
Date: 20251015
DEA Schedule: CIII

ACTIVE INGREDIENTS: BENZPHETAMINE HYDROCHLORIDE 50 mg/1 1
INACTIVE INGREDIENTS: CARNAUBA WAX; SILICON DIOXIDE; FD&C RED NO. 40; FD&C YELLOW NO. 6; LACTOSE MONOHYDRATE; POLYETHYLENE GLYCOL 3350; MAGNESIUM STEARATE; MICROCRYSTALLINE CELLULOSE; POLYVINYL ALCOHOL; SODIUM STARCH GLYCOLATE TYPE A POTATO; TALC; TITANIUM DIOXIDE

Benzphetamine Hydrochloride Tablets CIII
Rx Only

DESCRIPTION

Benzphetamine hydrochloride tablets contain the anorectic agent benzphetamine hydrochloride. Benzphetamine hydrochloride is a white crystalline powder readily soluble in water and 95% ethanol. The chemical name for benzphetamine hydrochloride is d-N,α-Dimethyl-N -(phenylmethyl)-benzeneethanamine hydrochloride and its molecular weight is 275.82.

The structural formula (dextro form) is represented below:

Each benzphetamine hydrochloride tablet, for oral administration, contains 50 mg of benzphetamine hydrochloride.

Inactive Ingredients: carnauba wax powder, colloidal silicon dioxide, FD&C red # 40 aluminum lake, FD&C yellow # 6 aluminum lake, lactose monohydrate, macrogol/polyethylene glycol 3350, magnesium stearate, microcrystalline cellulose 101, polyvinyl alcohol – partially hydrolyzed, sodium starch glycolate, talc and titanium dioxide.

CLINICAL PHARMACOLOGY

Benzphetamine hydrochloride is a sympathomimetic amine with pharmacologic activity similar to the prototype drugs of this class used in obesity, the amphetamines. Actions include central nervous system stimulation and elevation of blood pressure. Tachyphylaxis and tolerance have been demonstrated with all drugs of this class in which these phenomena have been looked for.

Drugs of this class used in obesity are commonly known as "anorectics" or "anorexigenics". It has not been established, however, that the action of such drugs in treating obesity is primarily one of appetite suppression. Other central nervous system actions, or metabolic effects, may be involved.

Adult obese subjects instructed in dietary management and treated with "anorectic" drugs, lose more weight on the average than those treated with placebo and diet, as determined in relatively short-term clinical trials.

The magnitude of increased weight loss of drug-treated patients over placebo-treated patients is only a fraction of a pound a week. The rate of weight loss is the greatest in the first weeks of therapy for both drug and placebo subjects and tends to decrease in succeeding weeks. The possible origins of the increased weight loss due to the various drug effects are not established. The amount of weight loss associated with the use of an "anorectic" drug varies from trial to trial, and the increased weight loss appears to be related in part to variables other than the drug prescribed, such as the physician-investigator, the population treated, and the diet prescribed. Studies do not permit conclusions as to the relative importance of the drug and non-drug factors on weight loss.

The natural history of obesity is measured in years, whereas the studies cited are restricted to a few weeks duration; thus, the total impact of drug-induced weight loss over that of diet alone must be considered to be clinically limited.

Pharmacokinetic data in humans are not available.

INDICATIONS AND USAGE

Benzphetamine hydrochloride tablets are indicated in the management of exogenous obesity as a short term (a few weeks) adjunct in a regimen of weight reduction based on caloric restriction in patients with an initial body mass index (BMI) of 30 kg/m2 or higher who have not responded to appropriate weight reducing regimen (diet and/or exercise) alone. Below is a chart of Body Mass Index (BMI) based on various heights and weights. BMI is calculated by taking the patient's weight, in kilograms (kg), divided by the patient's height, in meters (m), squared. Metric conversions are as follows: pounds ÷2.2 = kg; inches × 0.0254 = meters. The limited usefulness of agents of this class (See CLINICAL PHARMACOLOGY) should be weighed against possible risks inherent in their use such as those described below.

Benzphetamine hydrochloride tablets are indicated for use as monotherapy only.

CONTRAINDICATIONS

Benzphetamine hydrochloride tablets are contraindicated in patients with advanced arteriosclerosis, symptomatic cardiovascular disease, moderate to severe hypertension, hyperthyroidism, known hypersensitivity or idiosyncrasy to sympathomimetic amines, and glaucoma. Benzphetamine should not be given to patients who are in an agitated state or who have a history of drug abuse.

Hypertensive crises have resulted when sympathomimetic amines have been used concomitantly or within 14 days following use of monoamine oxidase inhibitors. Benzphetamine hydrochloride tablets should not be used concomitantly with other CNS stimulants.

Benzphetamine hydrochloride tablets may cause fetal harm when administered to a pregnant woman. Amphetamines have been shown to be teratogenic and embryotoxic in mammals at high multiples of the human dose. Benzphetamine hydrochloride tablets are contraindicated in women who are or may become pregnant. If this drug is used during pregnancy, or if the patient becomes pregnant while taking this drug, the patient should be apprised of the potential hazard to the fetus.

WARNINGS

Benzphetamine hydrochloride tablets should not be used in combination with other anorectic agents, including prescribed drugs, over-the-counter preparations and herbal products.

In a case-control epidemiological study, the use of anorectic agents was associated with an increased risk of developing pulmonary hypertension, a rare, but often fatal disorder. The use of anorectic agents for longer than three months was associated with a 23-fold increase in the risk of developing pulmonary hypertension. Increased risk of pulmonary hypertension with repeated courses of therapy cannot be excluded. It should be noted that benzphetamine was not specifically studied in this case-control study.

The onset or aggravation of exertional dyspnea, or unexplained symptoms of angina pectoris, syncope, or lower extremity edema suggest the possibility of occurrence of pulmonary hypertension. Under these circumstances, Benzphetamine hydrochloride tablets should be immediately discontinued, and the patient should be evaluated for the possible presence of pulmonary hypertension.

Valvular heart disease associated with the use of some anorectic agents such as fenfluramine and dexfenfluramine has been reported. Possible contributing factors include use for extended periods of time, higher than recommended dose, and/or use in combination with other anorectic drugs. However, no cases of this valvulopathy have been reported when benzphetamine has been used alone.

The potential risk of possible serious adverse effects such as valvular heart disease and pulmonary hypertension should be assessed carefully against the potential benefit of weight loss. Baseline cardiac evaluation should be considered to detect pre-existing valvular heart diseases or pulmonary hypertension prior to initiation of benzphetamine treatment. Benzphetamine hydrochloride tablets are not recommended in patients with known heart murmur or valvular heart disease. Echocardiogram during and after treatment could be useful for detecting any valvular disorders which may occur. To limit unwarranted exposure and risks, treatment with benzphetamine hydrochloride tablets should be continued only if the patient has satisfactory weight loss within the first 4 weeks of treatment (i.e., weight loss of at least 4 pounds, or as determined by the physician and patient).

When tolerance to the anorectic effect develops, the recommended dose should not be exceeded in an attempt to increase the effect; rather, the drug should be discontinued.

Benzphetamine hydrochloride tablets are not recommended for severely hypertensive patients or for patients with symptomatic cardiovascular disease including arrhythmias.

Benzphetamine hydrochloride tablets are not recommended for patients who used any anorectic agents within the prior year.

PRECAUTIONS

General

Insulin requirements in diabetes mellitus may be altered in association with use of anorexigenic drugs and the concomitant dietary restrictions.

Psychological disturbances have been reported in patients who receive an anorectic agent together with a restrictive dietary regime.

Caution is to be exercised in prescribing amphetamines for patients with even mild hypertension. The least amount feasible should be prescribed or dispensed at one time in order to minimize the possibility of overdosage.

Information for Patients

Amphetamines may impair the ability of the patient to engage in potentially hazardous activities such as operating machinery or driving a motor vehicle; the patient should therefore be cautioned accordingly.

Drug Interactions

Efficacy of benzphetamine hydrochloride tablets in combination with other anorectic agents has not been studied and the combined use may have the potential for serious cardiac problems.

Hypertensive crises have resulted when sympathomimetic amines have been used concomitantly or within 14 days following use of monoamine oxidase inhibitors. Benzphetamine hydrochloride tablets should not be used concomitantly with other CNS stimulants.

Amphetamines may decrease the hypotensive effect of antihypertensives. Amphetamines may enhance the effects of tricyclic antidepressants.

Urinary alkalinizing agents increase blood levels and decrease excretion of amphetamines. Urinary acidifying agents decrease blood levels and increase excretion of amphetamines.

Carcinogenesis, Mutagenesis, Impairment of Fertility

Animal studies to evaluate the potential for carcinogenesis, mutagenesis or impairment of fertility have not been performed by Pharmacia & Upjohn Company.

Pregnancy

Benzphetamine hydrochloride tablets are contraindicated in pregnancy.

Nursing Mothers

Amphetamines are excreted in human milk. Mothers taking amphetamines should be advised to refrain from nursing.

Pediatric Use

Safety and effectiveness in pediatric patients have not been established. The use of benzphetamine hydrochloride is not recommended in patients less than 17 years of age.

Geriatric Use

Clinical studies of benzphetamine hydrochloride tablets did not include sufficient numbers of subjects aged 65 and over to establish safety and efficacy in this population. In general, dose selection for an elderly patient should be cautious, usually starting at the low end of the dosing range, reflecting the greater frequency of decreased hepatic, renal, or cardiac function, and of concomitant disease or other drug therapy.

ADVERSE REACTIONS

The following have been associated with the use of benzphetamine hydrochloride:

Cardiovascular

Palpitation, tachycardia, elevation of blood pressure.

There have been isolated reports of cardiomyopathy and ischemic cardiac events associated with chronic amphetamine use.

Valvular heart disease associated with the use of some anorectic agents such as fenfluramine and dexfenfluramine, both independently and especially when used in combination with other anorectic drugs, have been reported. However, no cases of this valvulopathy have been reported when benzphetamine hydrochloride tablets have been used alone.

CNS

Overstimulation, restlessness, dizziness, insomnia, tremor, sweating, headache; rarely, psychotic episodes at recommended doses; depression following withdrawal of the drug.

Gastrointestinal

Dryness of the mouth, unpleasant taste, nausea, diarrhea, other gastrointestinal disturbances.

Allergic

Urticaria and other allergic reactions involving the skin.

Endocrine

Changes in libido.

DRUG ABUSE AND DEPENDENCE

Benzphetamine is a controlled substance under the Controlled Substance Act by the Drug Enforcement Administration and has been assigned to Schedule III.

Benzphetamine hydrochloride is related chemically and pharmacologically to the amphetamines. Amphetamines and related stimulant drugs have been extensively abused, and the possibility of abuse of benzphetamine hydrochloride tablets should be kept in mind when evaluating the desirability of including a drug as part of a weight reduction program. Abuse of amphetamines and related drugs may be associated with intense psychological dependence and severe social dysfunction. There are reports of patients who have increased the dosage to many times that recommended. Abrupt cessation following prolonged high dosage administration results in extreme fatigue and mental depression; changes are also noted on the sleep EEG. Manifestations of chronic intoxication with anorectic drugs include severe dermatoses, marked insomnia, irritability, hyperactivity, and personality changes. The most severe manifestation of chronic intoxication is psychosis, often clinically indistinguishable from schizophrenia.

OVERDOSAGE

Manifestations of Overdosage

Acute overdosage with amphetamines may result in restlessness, tremor, tachypnea, confusion, assaultiveness and panic states. Fatigue and depression usually follow the central stimulation. Cardiovascular effects include arrhythmias, hypertension or hypotension, and circulatory collapse. Gastrointestinal symptoms include nausea, vomiting, diarrhea, and abdominal cramps. Hyperpyrexia and rhabdomyolysis have been reported and can lead to a number of associated complications. Fatal poisoning is usually preceded by convulsions and coma.

Treatment of Overdosage

(See WARNINGS)--- Information concerning the effects of overdosage with benzphetamine hydrochloride tablets is extremely limited. The following is based on experience with other anorexiants.

Management of acute amphetamine intoxication is largely symptomatic and includes sedation with a barbiturate. If hypertension is marked, the use of a nitrite or rapidly acting alpha receptor blocking agent should be considered. Experience with hemodialysis or peritoneal dialysis is inadequate to permit recommendations in this regard.

Acidification of the urine increases amphetamine excretion.

The oral LD50is 174 mg/kg in mice and 104 mg/kg in rats. The intraperitoneal LD50in mice is 153 mg/kg.

DOSAGE AND ADMINISTRATION

Dosage should be individualized according to the response of the patient. The suggested dosage ranges from 25 to 50 mg one to three times daily. Treatment should begin with 25 to 50 mg once daily with subsequent increase in individual dose or frequency according to response. A single daily dose is preferably given in mid-morning or mid-afternoon, according to the patient’s eating habits. In an occasional patient it may be desirable to avoid late afternoon administration. Use of benzphetamine hydrochloride is not recommended in individuals under 17 years of age.

HOW SUPPLIED

Benzphetamine hydrochloride tablets are available as follows:

Benzphetamine hydrochloride tablets, 50 mg are supplied as peach, round, biconvex, film coated tablets debossed with “K” on left of the score and the number “40” debossed right of the score and plain on other side.

Bottles of 14 NDC 43063-541-14

Bottles of 30 NDC 43063-541-30

Bottles of 45 NDC 43063-541-45

Bottles of 60 NDC 43063-541-60

Bottles of 90 NDC 43063-541-90

Bottles of 120 NDC 43063-541-98

Dispensein a tight container as defined in the USP, with a child-resistant closure (as required).

Storeat 20° to 25°C with excursions permitted between 15° to 30°C (59° to 86°F) [see USP Controlled Room Temperature].

Rx only

PRINCIPAL DISPLAY PANEL

Benzphetamine Hydrochloride Tablets 50 mg CIII

Rx Only